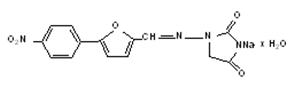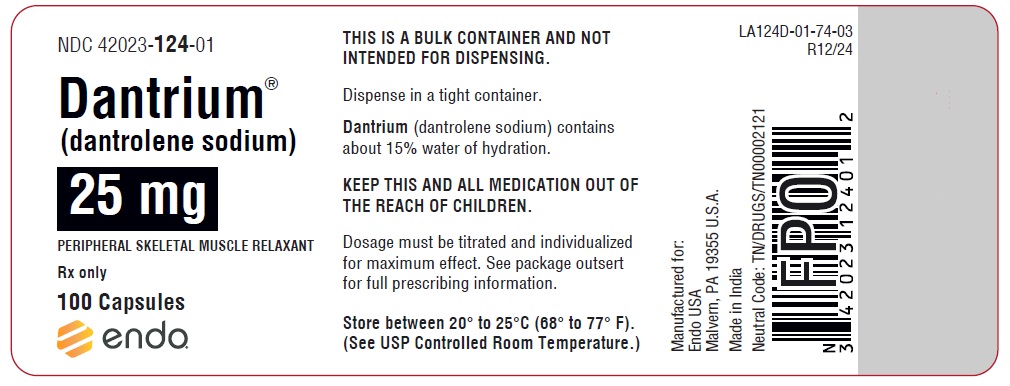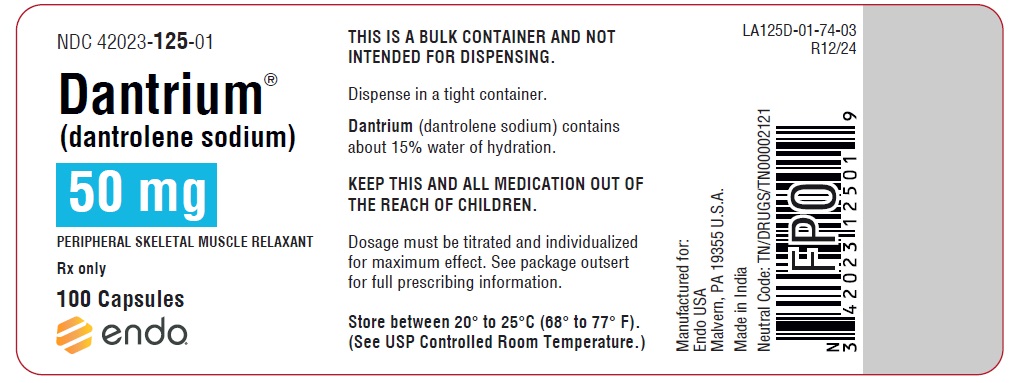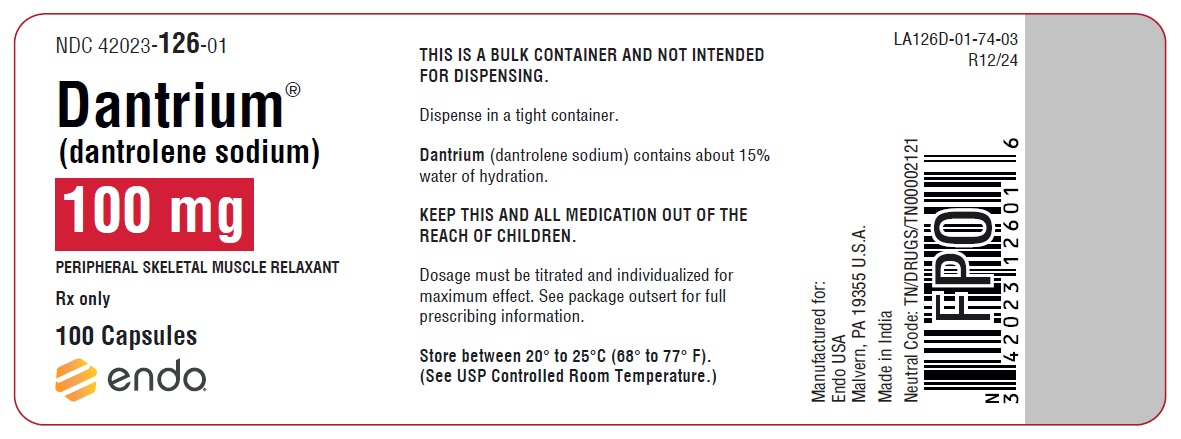 DRUG LABEL: Dantrium
NDC: 42023-124 | Form: CAPSULE
Manufacturer: Endo USA, Inc.
Category: prescription | Type: HUMAN PRESCRIPTION DRUG LABEL
Date: 20241219

ACTIVE INGREDIENTS: DANTROLENE SODIUM 25 mg/1 1
INACTIVE INGREDIENTS: FD&C YELLOW NO. 6; GELATIN; LACTOSE MONOHYDRATE; MAGNESIUM STEARATE; TALC; TITANIUM DIOXIDE; STARCH, CORN

Dantrium® Capsules
(dantrolene sodium)

BOXED WARNING

Dantrium (dantrolene sodium) has a potential for hepatotoxicity, and should not be used in conditions other than those recommended. Symptomatic hepatitis (fatal and non-fatal) has been reported at various dose levels of the drug. The incidence reported in patients taking up to 400 mg/day is much lower than in those taking doses of 800 mg or more per day. Even sporadic short courses of these higher dose levels within a treatment regimen markedly increased the risk of serious hepatic injury. Liver dysfunction as evidenced by blood chemical abnormalities alone (liver enzyme elevations) has been observed in patients exposed to Dantrium for varying periods of time. Overt hepatitis has occurred at varying intervals after initiation of therapy, but has been most frequently observed between the third and twelfth month of therapy. The risk of hepatic injury appears to be greater in females, in patients over 35 years of age, and in patients taking other medication(s) in addition to Dantrium (dantrolene sodium). Spontaneous reports suggest a higher proportion of hepatic events with fatal outcome in elderly patients receiving Dantrium. However, the majority of these cases were complicated with confounding factors such as intercurrent illnesses and/or concomitant potentially hepatotoxic medications (see Geriatric Use subsection). Dantrium should be used only in conjunction with appropriate monitoring of hepatic function including frequent determination of SGOT or SGPT. If no observable benefit is derived from the administration of Dantrium after a total of 45 days, therapy should be discontinued. The lowest possible effective dose for the individual patient should be prescribed.

DESCRIPTION

The chemical formula of Dantrium (dantrolene sodium) is hydrated 1-[[[5-(4-nitrophenyl)-2-furanyl]methylene]amino]-2, 4-imidazolidinedione sodium salt. It is an orange powder, slightly soluble in water, but due to its slightly acidic nature the solubility increases somewhat in alkaline solution. The anhydrous salt has a molecular weight of 336. The hydrated salt contains approximately 15% water (3-1/2 moles) and has a molecular weight of 399. The structural formula for the hydrated salt is:

Dantrium is supplied in capsules of 25 mg, 50 mg, and 100 mg.

Inactive Ingredients: Each capsule contains Edible black ink, FD&C Yellow No. 6, Gelatin, Lactose, Magnesium stearate, Starch, Synthetic iron oxide red, Synthetic iron oxide yellow, Talc, and Titanium dioxide.

CLINICAL PHARMACOLOGY

In isolated nerve-muscle preparation, Dantrium has been shown to produce relaxation by affecting the contractile response of the skeletal muscle at a site beyond the myoneural junction, directly on the muscle itself. In skeletal muscle, Dantrium dissociates the excitation-contraction coupling, probably by interfering with the release of Ca^++ from the sarcoplasmic reticulum. This effect appears to be more pronounced in fast muscle fibers as compared to slow ones, but generally affects both. A central nervous system effect occurs, with drowsiness, dizziness, and generalized weakness occasionally present. Although Dantrium does not appear to directly affect the CNS, the extent of its indirect effect is unknown. The absorption of Dantrium after oral administration in humans is incomplete and slow but consistent, and dose-related blood levels are obtained. The duration and intensity of skeletal muscle relaxation is related to the dosage and blood levels. The mean biologic half-life of Dantrium in adults is 8.7 hours after a 100-mg dose. Specific metabolic pathways in the degradation and elimination of Dantrium in human subjects have been established. Metabolic patterns are similar in adults and pediatric patients. In addition to the parent compound, dantrolene, which is found in measurable amounts in blood and urine, the major metabolites noted in body fluids are the 5-hydroxy analog and the acetamido analog. Since Dantrium is probably metabolized by hepatic microsomal enzymes, enhancement of its metabolism by other drugs is possible. However, neither phenobarbital nor diazepam appears to affect Dantrium metabolism.

Clinical experience in the management of fulminant human malignant hyperthermia, as well as experiments conducted in malignant hyperthermia susceptible swine, have revealed that the administration of intravenous dantrolene, combined with indicated supportive measures, is effective in reversing the hypermetabolic process of malignant hyperthermia. Known differences between human and swine malignant hyperthermia are minor. The prophylactic administration of oral or intravenous dantrolene to malignant hyperthermia susceptible swine will attenuate or prevent the development of signs of malignant hyperthermia in a manner dependent upon the dosage of dantrolene administered and the intensity of the malignant hyperthermia triggering stimulus. Limited clinical experience with the administration of oral dantrolene to patients judged malignant hyperthermia susceptible, when combined with clinical experience in the use of intravenous dantrolene for the treatment of malignant hyperthermia and data derived from the above cited animal model experiments, suggests that oral dantrolene will also attenuate or prevent the development of signs of human malignant hyperthermia, provided that currently accepted practices in the management of such patients are adhered to (see INDICATIONS AND USAGE); intravenous dantrolene should also be available for use should the signs of malignant hyperthermia appear.

INDICATIONS AND USAGE

In Chronic Spasticity:

Dantrium is indicated in controlling the manifestations of clinical spasticity resulting from upper motor neuron disorders (e.g., spinal cord injury, stroke, cerebral palsy, or multiple sclerosis). It is of particular benefit to the patient whose functional rehabilitation has been retarded by the sequelae of spasticity. Such patients must have presumably reversible spasticity where relief of spasticity will aid in restoring residual function. Dantrium is not indicated in the treatment of skeletal muscle spasm resulting from rheumatic disorders.

If improvement occurs, it will ordinarily occur within the dosage titration (see DOSAGE AND ADMINISTRATION), and will be manifested by a decrease in the severity of spasticity and the ability to resume a daily function not quite attainable without Dantrium.

Occasionally, subtle but meaningful improvement in spasticity may occur with Dantrium therapy. In such instances, information regarding improvement should be solicited from the patient and those who are in constant daily contact and attendance with him. Brief withdrawal of Dantrium for a period of 2 to 4 days will frequently demonstrate exacerbation of the manifestations of spasticity and may serve to confirm a clinical impression.

A decision to continue the administration of Dantrium on a long-term basis is justified if introduction of the drug into the patient's regimen:
produces a significant reduction in painful and/or disabling spasticity such as clonus, or
permits a significant reduction in the intensity and/or degree of nursing care required, or
rids the patient of any annoying manifestation of spasticity considered important by the patient himself.

In Malignant Hyperthermia:

Oral Dantrium is also indicated preoperatively to prevent or attenuate the development of signs of malignant hyperthermia in known, or strongly suspect, malignant hyperthermia susceptible patients who require anesthesia and/or surgery. Currently accepted clinical practices in the management of such patients must still be adhered to (careful monitoring for early signs of malignant hyperthermia, minimizing exposure to triggering mechanisms and prompt use of intravenous dantrolene sodium and indicated supportive measures should signs of malignant hyperthermia appear); see also the package insert for Dantrium® (dantrolene sodium) Intravenous.

Oral Dantrium should be administered following a malignant hyperthermic crisis to prevent recurrence of the signs of malignant hyperthermia.

CONTRAINDICATIONS

Active hepatic disease, such as hepatitis and cirrhosis, is a contraindication for use of Dantrium. Dantrium is contraindicated where spasticity is utilized to sustain upright posture and balance in locomotion or whenever spasticity is utilized to obtain or maintain increased function.

WARNINGS

It is important to recognize that fatal and non-fatal liver disorders of an idiosyncratic or hypersensitivity type may occur with Dantrium therapy.

At the start of Dantrium therapy, it is desirable to do liver function studies (SGOT, SGPT, alkaline phosphatase, total bilirubin) for a baseline or to establish whether there is pre-existing liver disease. If baseline liver abnormalities exist and are confirmed, there is a clear possibility that the potential for Dantrium hepatotoxicity could be enhanced, although such a possibility has not yet been established.

Liver function studies (e.g., SGOT or SGPT) should be performed at appropriate intervals during Dantrium therapy. If such studies reveal abnormal values, therapy should generally be discontinued. Only where benefits of the drug have been of major importance to the patient, should reinitiation or continuation of therapy be considered. Some patients have revealed a return to normal laboratory values in the face of continued therapy while others have not.

If symptoms compatible with hepatitis, accompanied by abnormalities in liver function tests or jaundice appear, Dantrium should be discontinued. If caused by Dantrium and detected early, the abnormalities in liver function characteristically have reverted to normal when the drug was discontinued. Dantrium therapy has been reinstituted in a few patients who have developed clinical and/or laboratory evidence of hepatocellular injury. If such reinstitution of therapy is done, it should be attempted only in patients who clearly need Dantrium and only after previous symptoms and laboratory abnormalities have cleared. The patient should be hospitalized and the drug should be restarted in very small and gradually increasing doses. Laboratory monitoring should be frequent and the drug should be withdrawn immediately if there is any indication of recurrent liver involvement. Some patients have reacted with unmistakable signs of liver abnormality upon administration of a challenge dose, while others have not.

Dantrium should be used with particular caution in females and in patients over 35 years of age in view of apparent greater likelihood of drug-induced, potentially fatal, hepatocellular disease in these groups. Spontaneous reports suggest a higher proportion of hepatic events with fatal outcome in elderly patients receiving Dantrium. However, the majority of these cases were complicated with confounding factors such as intercurrent illnesses and/or concomitant potentially hepatotoxic medications (see Geriatric Use subsection).

Carcinogenesis, Mutagenesis, Impairment of Fertility:

Long-term safety of Dantrium in humans has not been established. Chronic studies in rats, dogs, and monkeys at dosages greater than 30 mg/kg/day showed growth or weight depression and signs of hepatopathy and possible occlusion nephropathy, all of which were reversible upon cessation of treatment. Sprague-Dawley female rats fed dantrolene sodium for 18 months at dosage levels of 15, 30, and 60 mg/kg/day showed an increased incidence of benign and malignant mammary tumors compared with concurrent controls. At the highest dose level, there was an increase in the incidence of benign lymphatic neoplasms. In a 30-month study at the same dose levels also in Sprague-Dawley rats, dantrolene sodium produced a decrease in the time of onset of mammary neoplasms. Female rats at the highest dose level showed an increased incidence of hepatic lymphangiomas and hepatic angiosarcomas.

The only drug-related effect seen in a 30-month study in Fischer-344 rats was a dose-related reduction in the time of onset of mammary and testicular tumors. A 24-month study in HaM/ICR mice revealed no evidence of carcinogenic activity. Carcinogenicity in humans cannot be fully excluded, so that this possible risk of chronic administration must be weighed against the benefits of the drug (i.e., after a brief trial) for the individual patient.

Dantrolene sodium has produced positive results in the Ames S. Typhimurium bacterial mutagenesis assay in the presence and absence of a liver activating system.

Pregnancy:

Adequate animal reproduction studies have not been conducted with Dantrium. It is also not known whether Dantrium can cause fatal harm when administered to a pregnant woman or can affect reproduction capacity. Dantrium should be given to a pregnant woman only if clearly needed.

Labor and Delivery:

In one non-randomized open-label study, 21 term pregnant patients received prophylactic oral Dantrium 100 mg per day for 2 to 10 days prior to delivery. Dantrolene readily crossed the placenta with maternal and fetal whole blood levels approximately equal at delivery; neonatal levels then fell approximately 50% per day for 2 days before declining sharply. No neonatal respiratory and neuromuscular side effects were detected at low dose. More data, at higher doses, are needed before more definitive conclusions can be made.

Nursing Mothers:

Dantrium should not be used in nursing mothers.

Usage in Pediatric Patients:

The long-term safety of Dantrium in pediatric patients under the age of 5 years has not been established. Because of the possibility that adverse effects of the drug could become apparent only after many years, a benefit-risk consideration of the long-term use of Dantrium is particularly important in pediatric patients.

Geriatric Use:

Clinical studies of Dantrium did not include sufficient numbers of subjects aged 65 and over to determine whether they respond differently from younger subjects. Other reported clinical experience in the literature has not identified differences in responses between the elderly and younger patients. In general, dose selection for an elderly patient should be cautious, reflecting the greater frequency of decreased hepatic, renal, or cardiac function, and of concomitant disease or other drug therapy. As with all patients receiving Dantrium, it is recommended that elderly patients receive the lowest dose compatible with the optimal response. Spontaneous reports suggest a higher proportion of hepatic events with fatal outcome in elderly patients receiving Dantrium. However, the majority of these cases were complicated with confounding factors such as intercurrent illnesses and/or concomitant potentially hepatotoxic medications (for hepatotoxicity details and its management see Black Box and Warnings Sections).

Drug Interactions:

Drowsiness may occur with Dantrium therapy, and the concomitant administration of CNS depressants such as sedatives and tranquilizing agents may result in further drowsiness.

While a definite drug interaction with estrogen therapy has not yet been established, caution should be observed if the two drugs are to be given concomitantly. Hepatotoxicity has occurred more often in women over 35 years of age receiving concomitant estrogen therapy.

Cardiovascular collapse in patients treated simultaneously with verapamil and dantrolene sodium is rare. The combination of therapeutic doses of intravenous dantrolene sodium and verapamil in halothane/α-chloralose anesthetized swine has resulted in ventricular fibrillation and cardiovascular collapse in association with marked hyperkalemia. Until the relevance of these findings to humans is established, the combination of dantrolene sodium and calcium channel blockers is not recommended during the management of malignant hyperthermia.

Administration of Dantrium may potentiate vecuronium-induced neuromuscular block.

PRECAUTIONS

Dantrium should be used with caution in patients with impaired pulmonary function, particularly those with obstructive pulmonary disease, and in patients with severely impaired cardiac function due to myocardial disease. Dantrium is associated with pleural effusion with associated eosinophilia. It should be used with caution in patients with a history of previous liver disease or dysfunction (see WARNINGS).

Information for Patients:

Patients should be cautioned against driving a motor vehicle or participating in hazardous occupations while taking Dantrium. Caution should be exercised in the concomitant administration of tranquilizing agents.

Dantrium might possibly evoke a photosensitivity reaction; patients should be cautioned about exposure to sunlight while taking it.

ADVERSE REACTIONS

The most frequently occurring side effects of Dantrium have been drowsiness, dizziness, weakness, general malaise, fatigue, and diarrhea. These are generally transient, occurring early in treatment, and can often be obviated by beginning with a low dose and increasing dosage gradually until an optimal regimen is established. Diarrhea may be severe and may necessitate temporary withdrawal of Dantrium therapy. If diarrhea recurs upon readministration of Dantrium, therapy should probably be withdrawn permanently.

Other less frequent side effects, listed according to system, are:

Gastrointestinal: Constipation, rarely progressing to signs of intestinal obstruction, GI bleeding, anorexia, swallowing difficulty, gastric irritation, abdominal cramps, nausea and/or vomiting.

Hepatobiliary: Hepatitis (see WARNINGS).

Neurologic: Speech disturbance, seizure, headache, light-headedness, visual disturbance, diplopia, alteration of taste, insomnia, drooling.

Cardiovascular: Tachycardia, erratic blood pressure, phlebitis, heart failure.

Hematologic: Aplastic anemia, anemia, leukopenia, lymphocytic lymphoma, thrombocytopenia.

Psychiatric: Mental depression, mental confusion, increased nervousness.

Urogenital: Increased urinary frequency, crystalluria, hematuria, difficult erection, urinary incontinence and/or nocturia, difficult urination and/or urinary retention.

Integumentary: Abnormal hair growth, acne-like rash, pruritus, urticaria, eczematoid eruption, sweating.

Musculoskeletal: Myalgia, backache.

Respiratory: Feeling of suffocation, respiratory depression.

Special Senses: Excessive tearing.

Hypersensitivity: Pleural effusion with pericarditis, pleural effusion with associated eosinophilia, anaphylaxis.

Other: Chills and fever.

The published literature has included some reports of Dantrium use in patients with Neuroleptic Malignant Syndrome (NMS). Dantrium capsules are not indicated for the treatment of NMS and patients may expire despite treatment with Dantrium capsules.

For medical advice about adverse reactions contact your medical professional. To report SUSPECTED ADVERSE REACTIONS, contact Endo, at
1-800-828-9393 or FDA at 1-800-FDA-1088 or www.fda.gov/medwatch.

DRUG ABUSE AND DEPENDENCE

Drug abuse and dependency potential has not been evaluated in human or animal studies.

OVERDOSAGE

Symptoms which may occur in case of overdose include, but are not limited to, muscular weakness and alterations in the state of consciousness (e.g. lethargy, coma), vomiting, diarrhea, and crystalluria. For acute overdose, general supportive measures should be employed along with immediate gastric lavage.

Intravenous fluids should be administered in fairly large quantities to avert the possibility of crystalluria. An adequate airway should be maintained and artificial resuscitation equipment should be at hand. Electrocardiographic monitoring should be instituted, and the patient carefully observed. To date, no experience has been reported with dialysis and its value in Dantrium overdose is not known.

DOSAGE AND ADMINISTRATION

For Use in Chronic Spasticity:

Prior to the administration of Dantrium, consideration should be given to the potential response to treatment. A decrease in spasticity sufficient to allow a daily function not otherwise attainable should be the therapeutic goal of treatment with Dantrium. Refer to INDICATIONS AND USAGE section for description of response to be anticipated.

It is important to establish a therapeutic goal (regain and maintain a specific function such as therapeutic exercise program, utilization of braces, transfer maneuvers, etc.) before beginning Dantrium therapy. Dosage should be increased until the maximum performance compatible with the dysfunction due to underlying disease is achieved. No further increase in dosage is then indicated.

Usual Dosage:

It is important that the dosage be titrated and individualized for maximum effect. The lowest dose compatible with optimal response is recommended.

In view of the potential for liver damage in long-term Dantrium use, therapy should be stopped if benefits are not evident within 45 days.

Adults:

The following gradual titration schedule is suggested. Some patients will not respond until higher daily dosage is achieved. Each dosage level should be maintained for seven days to determine the patient's response. If no further benefit is observed at the next higher dose, dosage should be decreased to the previous lower dose.

25 mg once daily for seven days, then

25 mg t.i.d. for seven days

50 mg t.i.d. for seven days

100 mg t.i.d.

Therapy with a dose four times daily may be necessary for some individuals. Doses higher than 100 mg four times daily should not be used. (See Box Warning.)

Pediatric Patients:

The following gradual titration schedule is suggested. Some patients will not respond until higher daily dosage is achieved. Each dosage level should be maintained for seven days to determine the patient's response. If no further benefit is observed at the next higher dose, dosage should be decreased to the previous lower dose.

0.5 mg/kg once daily for seven days, then

0.5 mg/kg t.i.d. for seven days

1 mg/kg t.i.d. for seven days

2 mg/kg t.i.d.

Therapy with a dose four times daily may be necessary for some individuals. Doses higher than 100 mg four times daily should not be used. (See Box Warning.)

For Malignant Hyperthermia:

Preoperatively: Administer 4 to 8 mg/kg/day of oral Dantrium in 3 or 4 divided doses for one or two days prior to surgery, with the last dose being given approximately 3 to 4 hours before scheduled surgery with a minimum of water.

This dosage will usually be associated with skeletal muscle weakness and sedation (sleepiness or drowsiness); adjustment can usually be made within the recommended dosage range to avoid incapacitation or excessive gastrointestinal irritation (including nausea and/or vomiting).

Post Crisis Follow-up: Oral Dantrium should also be administered following a malignant hyperthermia crisis, in doses of 4 to 8 mg/kg per day in four divided doses, for a one to three day period to prevent recurrence of the manifestations of malignant hyperthermia.

HOW SUPPLIED:

Dantrium (dantrolene sodium) is available in:

25-mg opaque, orange and tan capsules imprinted with DANTRIUM 25 mg on the cap and 0149 0030 with a single bar on the body.
NDC 42023-124-01 bottle of 100

50-mg opaque, orange and tan capsules imprinted with DANTRIUM 50 mg on the cap and 0149 0031 with a double bar on the body.
NDC 42023-125-01 bottle of 100

100-mg opaque, orange and tan capsules imprinted with DANTRIUM 100 mg on the cap and 0149 0033 with a triple bar on the body.
NDC 42023-126-01 bottle of 100

STORAGE AND HANDLING

Store between 20° to 25°C (68° to 77°F) [See USP Controlled Room Temperature].

Rx Only.

Manufactured for:

Endo USA

Malvern, PA 19355 U.S.A.

Made in India

Neutral Code: TN/DRUGS/TN00002121

© 2024 Endo, Inc. or one of its affiliates.

OS124D-01-74-03

Revised: 12/2024

PRINCIPAL DISPLAY PANEL - 25 mg Bottle Label

NDC 42023-124-01

25 mg

Dantrium®
(dantrolene sodium)

PERIPHERAL SKELETAL MUSCLE RELAXANT

100 Capsules
Rx only

PRINCIPAL DISPLAY PANEL - 50 mg Bottle label

NDC 42023-125-01

50 mg

Dantrium®
(dantrolene sodium)

PERIPHERAL SKELETAL MUSCLE RELAXANT

100 Capsules
Rx only

PRINCIPAL DISPLAY PANEL - 100 mg Bottle Label

NDC 42023-126-01

100 mg

Dantrium®
(dantrolene sodium)

PERIPHERAL SKELETAL MUSCLE RELAXANT

100 Capsules
Rx only